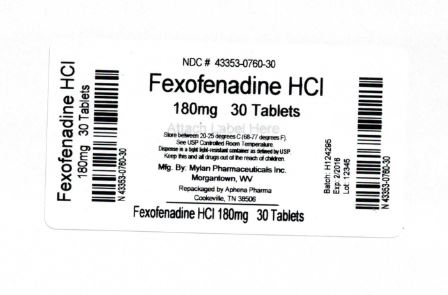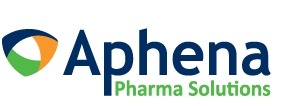 DRUG LABEL: Fexofenadine Hydrochloride
NDC: 43353-760 | Form: TABLET, FILM COATED
Manufacturer: Aphena Pharma Solutions - Tennessee, LLC
Category: otc | Type: HUMAN OTC DRUG LABEL
Date: 20171201

ACTIVE INGREDIENTS: FEXOFENADINE HYDROCHLORIDE 180 mg/1 1
INACTIVE INGREDIENTS: BUTYLATED HYDROXYANISOLE; CROSPOVIDONE (15 MPA.S AT 5%); FD&C BLUE NO. 1; HYPROMELLOSE, UNSPECIFIED; LACTOSE MONOHYDRATE; MAGNESIUM STEARATE; MICROCRYSTALLINE CELLULOSE; POLYDEXTROSE; POLYETHYLENE GLYCOL, UNSPECIFIED; POLYSORBATE 80; POVIDONE, UNSPECIFIED; SODIUM LAURYL SULFATE; TITANIUM DIOXIDE; TRIACETIN

Drug Facts

Active ingredient (in each tablet)

Fexofenadine hydrochloride USP, 60 mg

Purpose

Antihistamine

Uses

temporarily relieves these symptoms due to hay fever or other upper respiratory allergies:

- runny nose
- sneezing
- itchy, watery eyes
- itching of the nose or throat

Warnings

Do not use

if you have ever had an allergic reaction to this product or any of its ingredients.

Ask a doctor before use if you have

kidney disease. Your doctor should determine if you need a different dose.

When using this product

- do not take more than directed
- do not take at the same time as aluminum or magnesium antacids
- do not take with fruit juices (see Directions)

Stop use and ask a doctor if

an allergic reaction to this product occurs. Seek medical help right away.

If pregnant or breast-feeding,

ask a health professional before use.

Keep out of reach of children.

In case of overdose, get medical help or contact a Poison Control Center right away.

Directions

adults and children 12 years of age and over | take one 60 mg tablet with water every 12 hours; do not take more than 2 tablets in 24 hours
children under 12 years of age | do not use
adults 65 years of age and older | ask a doctor
consumers with kidney disease | ask a doctor

Other information

- Tamper Evident: do not use if foil seal under cap is missing, open or broken
- store between 20° to 25°C (68° to 77°F)
- protect from excessive moisture

Inactive ingredients

Butylated hydroxyanisole, crospovidone, FD&C Blue No. 1 Aluminum Lake, hypromellose, lactose monohydrate, magnesium stearate, microcrystalline cellulose, polydextrose, polyethylene glycol, polysorbate 80, povidone, sodium lauryl sulfate, titanium dioxide and triacetin.

Questions or comments?

Call 1-877-446-3679 (1-877-4-INFO-RX)

Manufactured by: Mylan Pharmaceuticals Inc., Morgantown, WV 26505 U.S.A.
Marketed/ Packaged by: GSMS, Inc., Camarillo, CA 93012 USA

Repackaging Information

Please reference the How Supplied section listed above for a description of individual tablets. This drug product has been received by Aphena Pharma - TN in a manufacturer or distributor packaged configuration and repackaged in full compliance with all applicable cGMP regulations. The package configurations available from Aphena are listed below:

Count | 180 mg
30 | 43353-760-30
60 | 43353-760-53
90 | XXXXX-XXX-60
120 | XXXXX-XXX-70
180 | XXXXX-XXX-80
240 | XXXXX-XXX-90
270 | XXXXX-XXX-92

Store between 20°-25°C (68°-77°F). See USP Controlled Room Temperature. Dispense in a tight light-resistant container as defined by USP. Keep this and all drugs out of the reach of children.

Repackaged by:
Cookeville, TN 38506
20171201JH

PRINCIPAL DISPLAY PANEL - 180mg

NDC 43353-760 - Fexofenadine HCl 180mg - Rx Only